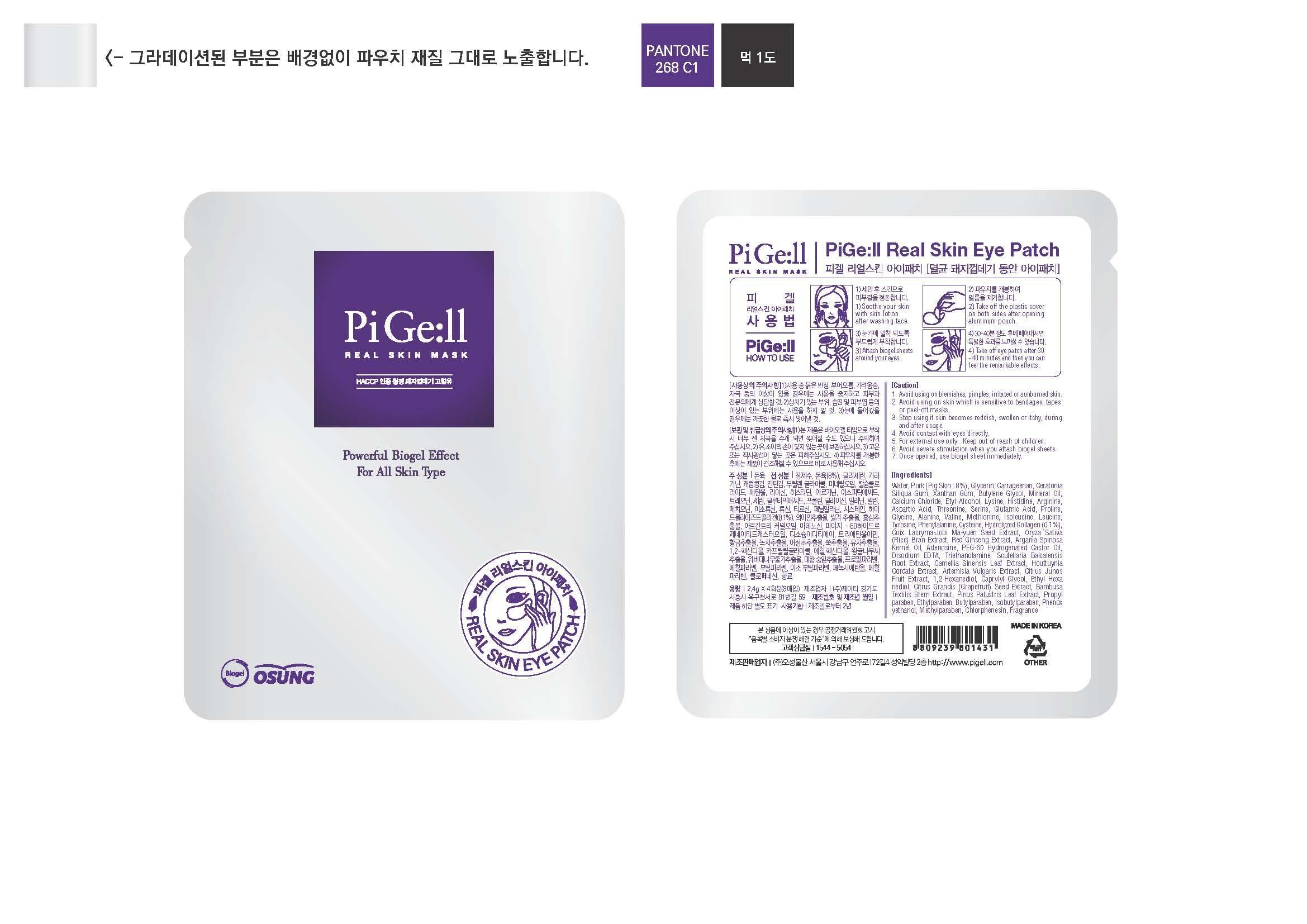 DRUG LABEL: PiGe ll Real Skin Eye
NDC: 55282-3001 | Form: PATCH
Manufacturer: Osung Co., Ltd
Category: otc | Type: HUMAN OTC DRUG LABEL
Date: 20130114

ACTIVE INGREDIENTS: SUS SCROFA SKIN 8 g/100 g
INACTIVE INGREDIENTS: METHYLISOTHIAZOLINONE; WATER; GLYCERIN; CARRAGEENAN; CERATONIA SILIQUA WHOLE; XANTHAN GUM; BUTYLENE GLYCOL; MINERAL OIL; CALCIUM CHLORIDE; ALCOHOL; LYSINE; HISTIDINE; ARGININE; ASPARTIC ACID; THREONINE; SERINE; GLUTAMIC ACID; PROLINE; GLYCINE; ALANINE; VALINE; METHIONINE; ISOLEUCINE; LEUCINE; TYROSINE; PHENYLALANINE; CYSTEINE; COIX LACRYMA-JOBI SEED OIL; ORYZA SATIVA WHOLE; PANAX GINSENG ROOT OIL; ARGAN OIL; ADENOSINE; POLYOXYL 60 HYDROGENATED CASTOR OIL; EDETATE DISODIUM; TROLAMINE; SCUTELLARIA BAICALENSIS ROOT; TEA LEAF OIL; HOUTTUYNIA CORDATA FLOWERING TOP; ARTEMISIA VULGARIS ROOT; CITRUS JUNOS FRUIT; 1,2-HEXANEDIOL; CAPRYLYL GLYCOL; ETHOHEXADIOL; CITRUS MAXIMA SEED; BAMBUSA TEXTILIS STEM; PINUS PALUSTRIS LEAF; PROPYLPARABEN; ETHYLPARABEN; BUTYLPARABEN; ISOBUTYLPARABEN; PHENOXYETHANOL; METHYLPARABEN; CHLORPHENESIN

Drug Facts

ACTIVE INGREDIENT

pork skin

INACTIVE INGREDIENT

Water, Glycerin, Carrageenan, Ceratonia Siliqua Gum, Xanthan Gum, Butylene Glycol, Mineral Oil, Calcium Chloride, Etyl Alcohol, Lysine, Histidine, Arginine, Aspartic Acid, Threonine, Serine, Glutamic Acid, Proline, Glycine, Alanine, Valine, Methionine, Isoleucine, Leucine, Tyrosine, Phenylalanine, Cysteine, Hydrolyzed Collagen (0.1%), Coix Lacryma-Jobi Ma-yuen Seed Extract, Oryza Sativa (Rice) Bran Extract, Red Ginseng Extract, Argania Spinosa Kernel Oil, Adenosine, PEG-60 Hydrogenated Castor Oil, Disodium EDTA, Triethanolamine, Scutellaria Baicalensis Root Extract, Camellia Sinensis Leaf Extract, Houttuynia Cordata Extract, Artemisia Vulgaris Extract, Citrus Junos Fruit Extract, 1,2-Hexanediol, Caprylyl Glycol, Ethyl Hexanediol, Citrus Grandis (Grapefruit) Seed Extract, Bambusa Textilis Stem Extract, Pinus Palustris Leaf Extract, Propylparaben, Ethylparaben, Butylparaben, Isobutylparaben, Phenoxyethanol, Methylparaben, Chlorphenesin, Fragrance

PURPOSE

for the treatment of skin

keep out or reach of the children

INDICATIONS AND USAGE

attach biogel sheets around your eyes

WARNINGS

■ Avoid using on blemishes, pimples, irritated or sunburned skin.
■ Avoid using on skin which is sensitive to bandages, tapes or peel-off masks.
■ Stop using if skin becomes reddish, swollen or itchy, during and after usage.
■ Avoid contact with eyes directly.

DOSAGE AND ADMINISTRATION

for external use only